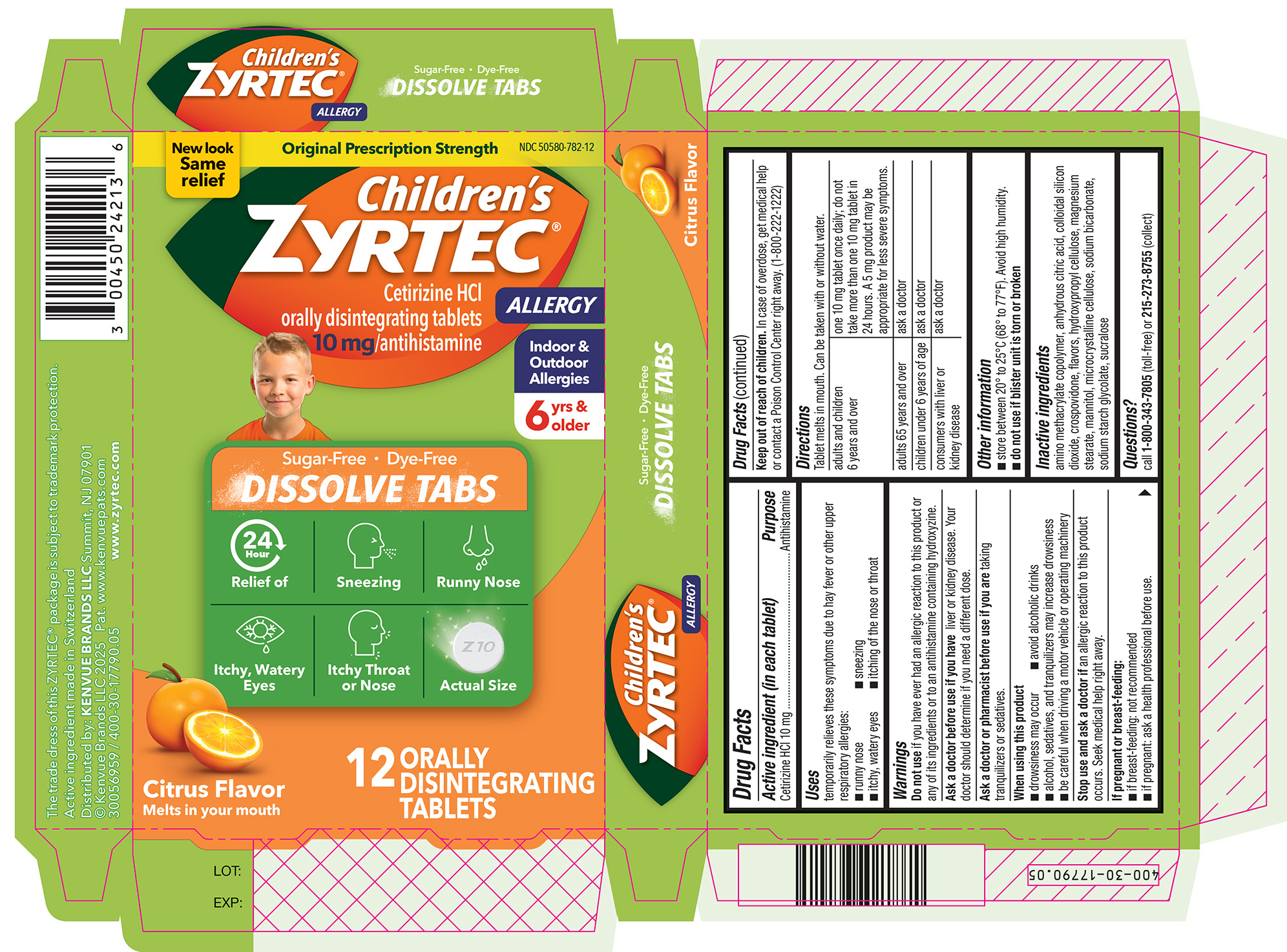 DRUG LABEL: Childrens Zyrtec Allergy
NDC: 50580-782 | Form: TABLET, ORALLY DISINTEGRATING
Manufacturer: Kenvue Brands LLC
Category: otc | Type: HUMAN OTC DRUG LABEL
Date: 20250422

ACTIVE INGREDIENTS: CETIRIZINE HYDROCHLORIDE 10 mg/1 1
INACTIVE INGREDIENTS: DIMETHYLAMINOETHYL METHACRYLATE - BUTYL METHACRYLATE - METHYL METHACRYLATE COPOLYMER; ANHYDROUS CITRIC ACID; SILICON DIOXIDE; CROSPOVIDONE; HYDROXYPROPYL CELLULOSE, UNSPECIFIED; MAGNESIUM STEARATE; MANNITOL; MICROCRYSTALLINE CELLULOSE; SODIUM BICARBONATE; SODIUM STARCH GLYCOLATE TYPE A; SUCRALOSE

Childrens Zyrtec Allergy

Drug Facts

Active ingredient (in each tablet)

Cetirizine HCl 10 mg

Purpose

Antihistamine

Uses

temporarily relieves these symptoms due to hay fever or other upper respiratory allergies:

- runny nose
- sneezing
- itchy, watery eyes
- itching of the nose or throat

Warnings

Do not use if you have ever had an allergic reaction to this product or any of its ingredients or to an antihistamine containing hydroxyzine.

Ask a doctor before use if you have liver or kidney disease. Your doctor should determine if you need a different dose.

Ask a doctor or pharmacist before use if you are taking tranquilizers or sedatives.

When using this product

- drowsiness may occur
- avoid alcoholic drinks
- alcohol, sedatives, and tranquilizers may increase drowsiness
- be careful when driving a motor vehicle or operating machinery

Stop use and ask a doctor if an allergic reaction to this product occurs. Seek medical help right away.

If pregnant or breast-feeding

- if breast-feeding: not recommended
- if pregnant: ask a health professional before use.

Keep out of reach of children. In case of overdose, get medical help or contact a Poison Control Center right away. (1-800-222-1222)

Directions

Tablet melts in mouth. Can be taken with or without water.

adults and children 6 years and over | one 10 mg tablet once daily; do not take more than one 10 mg tablet in 24 hours. A 5 mg product may be appropriate for less severe symptoms.
adults 65 years and over | ask a doctor
children under 6 years of age | ask a doctor
consumers with liver or kidney disease | ask a doctor

Other information

- store between 20° to 25°C (68° to 77°F). Avoid high humidity.
- do not use if blister unit is torn or broken

Inactive ingredients

amino methacrylate copolymer, anhydrous citric acid, colloidal silicon dioxide, crospovidone, flavors, hydroxypropyl cellulose, magnesium stearate, mannitol, microcrystalline cellulose, sodium bicarbonate, sodium starch glycolate, sucralose

Questions?

call 1-800-343-7805 (toll-free) or 215-273-8755 (collect)

PRINCIPAL DISPLAY PANEL

New look

Same

relief

Original Prescription Strength

NDC 50580-782-12

Children's
ZYRTEC®

ALLERGY

Cetirizine HCl

orally disintegrating tablets
10 mg/antihistamine

Indoor &

Outdoor

Allergies

6 yrs & older

Sugar-Free • Dye-Free

DISSOLVE TABS

24
Hour

Relief of

- Sneezing
- Runny Nose
- Itchy, Watery Eyes
- Itchy Throat or Nose

Actual Size

Citrus Flavor

Melts in your mouth

12 ORALLY DISINTEGRATING TABLETS